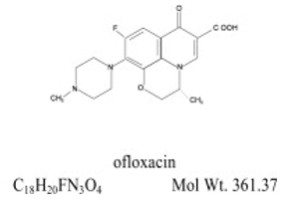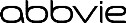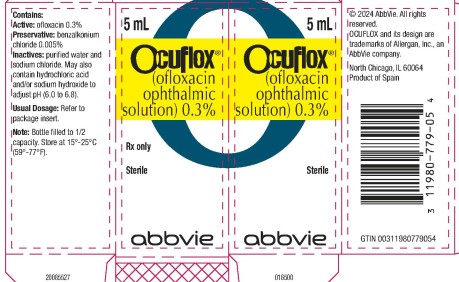 DRUG LABEL: OCUFLOX
NDC: 11980-779 | Form: SOLUTION/ DROPS
Manufacturer: Allergan, Inc.
Category: prescription | Type: HUMAN PRESCRIPTION DRUG LABEL
Date: 20240613

ACTIVE INGREDIENTS: ofloxacin 3 mg/1 mL
INACTIVE INGREDIENTS: BENZALKONIUM CHLORIDE; SODIUM CHLORIDE; WATER; HYDROCHLORIC ACID; SODIUM HYDROXIDE

OCUFLOX®
(ofloxacin ophthalmic solution) 0.3%
sterile

DESCRIPTION

OCUFLOX® (ofloxacin ophthalmic solution) 0.3% is a sterile ophthalmic solution. It is a fluorinated carboxyquinolone anti-infective for topical ophthalmic use.

Chemical Name:

(±)-9-Fluoro-2,3-dihydro-3-methyl-10-(4-methyl-1-piperazinyl)-7-oxo-7H-pyrido[1,2,3-de]-1,4-benzoxazine-6-carboxylic acid.

Contains: Active: ofloxacin 0.3% (3 mg/mL). Preservative: benzalkonium chloride (0.005%).

Inactives: sodium chloride and purified water. May also contain hydrochloric acid and/or sodium hydroxide to adjust pH.

OCUFLOX® solution is unbuffered and formulated with a pH of 6.4 (range - 6.0 to 6.8). It has an osmolality of 300 mOsm/kg. Ofloxacin is a fluorinated 4-quinolone which differs from other fluorinated 4-quinolones in that there is a six member (pyridobenzoxazine) ring from positions 1 to 8 of the basic ring structure.

CLINICAL PHARMACOLOGY

Pharmacokinetics

Serum, urine and tear concentrations of ofloxacin were measured in 30 healthy women at various time points during a ten-day course of treatment with OCUFLOX® solution. The mean serum ofloxacin concentration ranged from 0.4 ng/mL to 1.9 ng/mL. Maximum ofloxacin concentration increased from 1.1 ng/mL on day one to 1.9 ng/mL on day 11 after QID dosing for 10 1/2 days. Maximum serum ofloxacin concentrations after ten days of topical ophthalmic dosing were more than 1000 times lower than those reported after standard oral doses of ofloxacin.

Tear ofloxacin concentrations ranged from 5.7 to 31 mcg/g during the 40 minute period following the last dose on day 11. Mean tear concentration measured four hours after topical ophthalmic dosing was 9.2 mcg/g.

Corneal tissue concentrations of 4.4 mcg/mL were observed four hours after beginning topical ocular application of two drops of OCUFLOX® ophthalmic solution every 30 minutes. Ofloxacin was excreted in the urine primarily unmodified.

Microbiology

Ofloxacin has in vitro activity against a broad range of gram-positive and gram-negative aerobic and anaerobic bacteria. Ofloxacin is bactericidal at concentrations equal to or slightly greater than inhibitory concentrations. Ofloxacin is thought to exert a bactericidal effect on susceptible bacterial cells by inhibiting DNA gyrase, an essential bacterial enzyme which is a critical catalyst in the duplication, transcription, and repair of bacterial DNA.

Cross-resistance has been observed between ofloxacin and other fluoroquinolones. There is generally no cross-resistance between ofloxacin and other classes of antibacterial agents such as beta-lactams or aminoglycosides.

Ofloxacin has been shown to be active against most strains of the following organisms both in vitro and clinically, in conjunctival and/or corneal ulcer infections (see Indications and Usage).

AEROBES, GRAM-POSITIVE: | AEROBES, GRAM-NEGATIVE:
Staphylococcus aureus | Enterobacter cloacae
Staphylococcus epidermidis | Haemophilus influenzae
Streptococcus pneumoniae | Proteus mirabilis
ANAEROBIC SPECIES: | Pseudomonas aeruginosa
Propionibacterium acnes | Serratia marcescens*

*Efficacy for this organism was studied in fewer than 10 infections

The safety and effectiveness of OCUFLOX® ophthalmic solution in treating ophthalmologic infections due to the following organisms have not been established in adequate and well-controlled clinical trials. OCUFLOX® ophthalmic solution has been shown to be active in vitro against most strains of these organisms but the clinical significance in ophthalmologic infections is unknown.

AEROBES, GRAM-POSITIVE:
Enterococcus faecalis | Staphylococcus hominus
Listeria monocytogenes | Staphylococcus simulans
Staphylococcus capitis | Streptococcus pyogenes
AEROBES, GRAM-NEGATIVE:
Acinetobacter calcoaceticus var. anitratus | Klebsiella pneumoniae
Acinetobacter calcoaceticus var. lwoffii | Moraxella (Branhamella) catarrhalis
Citrobacter diversus | Moraxella lacunata
Citrobacter freundii | Morganella morganii
Enterobacter aerogenes | Neisseria gonorrhoeae
Enterobacter agglomerans | Pseudomonas acidovorans
Escherichia coli | Pseudomonas fluorescens
Haemophilus parainfluenzae | Shigella sonnei
Klebsiella oxytoca
OTHER:
Chlamydia trachomatis

Clinical Studies

Conjunctivitis

In a randomized, double-masked, multicenter clinical trial, OCUFLOX® ophthalmic solution was superior to its vehicle after 2 days of treatment in patients with conjunctivitis and positive conjunctival cultures. Clinical outcomes for the trial demonstrated a clinical improvement rate of 86% (54/63) for the ofloxacin treated group versus 72% (48/67) for the placebo treated group after 2 days of therapy. Microbiological outcomes for the same clinical trial demonstrated an eradication rate for causative pathogens of 65% (41/63) for the ofloxacin treated group versus 25% (17/67) for the vehicle treated group after 2 days of therapy. Please note that microbiologic eradication does not always correlate with clinical outcome in anti-infective trials.

Corneal Ulcers

In a randomized, double-masked, multi-center clinical trial of 140 subjects with positive cultures, OCUFLOX® ophthalmic solution treated subjects had an overall clinical success rate (complete re-epithelialization and no progression of the infiltrate for two consecutive visits) of 82% (61/74) compared to 80% (53/66) for the fortified antibiotic group, consisting of 1.5% tobramycin and 10% cefazolin solutions. The median time to clinical success was 11 days for the ofloxacin treated group and 10 days for the fortified treatment group.

INDICATIONS AND USAGE

OCUFLOX® ophthalmic solution is indicated for the treatment of infections caused by susceptible strains of the following bacteria in the conditions listed below:

CONJUNCTIVITIS:
Gram-positive bacteria: | Gram-negative bacteria:
Staphylococcus aureus | Enterobacter cloacae
Staphylococcus epidermidis | Haemophilus influenzae
Streptococcus pneumoniae | Proteus mirabilis
 | Pseudomonas aeruginosa
CORNEAL ULCERS:
Gram-positive bacteria: | Gram-negative bacteria:
Staphylococcus aureus | Pseudomonas aeruginosa
Staphylococcus epidermidis | Serratia marcescens*
Streptococcus pneumoniae | Anaerobic species:
 | Propionibacterium acnes

*Efficacy for this organism was studied in fewer than 10 infections

CONTRAINDICATIONS

OCUFLOX® solution is contraindicated in patients with a history of hypersensitivity to ofloxacin, to other quinolones, or to any of the components in this medication (see Warnings).

WARNINGS

NOT FOR INJECTION.

OCUFLOX® solution should not be injected subconjunctivally, nor should it be introduced directly into the anterior chamber of the eye.

There are rare reports of anaphylactic reaction/shock and fatal hypersensitivity reactions in patients receiving systemic quinolones, some following the first dose, including ofloxacin. Some reactions were accompanied by cardiovascular collapse, loss of consciousness, angioedema (including laryngeal, pharyngeal or facial edema), airway obstruction, dyspnea, urticaria, and itching. A rare occurrence of Stevens-Johnson syndrome, which progressed to toxic epidermal necrolysis, has been reported in a patient who was receiving topical ophthalmic ofloxacin. If an allergic reaction to ofloxacin occurs, discontinue the drug. Serious acute hypersensitivity reactions may require immediate emergency treatment. Oxygen and airway management, including intubation should be administered as clinically indicated.

PRECAUTIONS

General

As with other anti-infectives, prolonged use may result in overgrowth of nonsusceptible organisms, including fungi. If superinfection occurs discontinue use and institute alternative therapy. Whenever clinical judgment dictates, the patient should be examined with the aid of magnification, such as slit lamp biomicroscopy and, where appropriate, fluorescein staining. Ofloxacin should be discontinued at the first appearance of a skin rash or any other sign of hypersensitivity reaction.

The systemic administration of quinolones, including ofloxacin, has led to lesions or erosions of the cartilage in weight-bearing joints and other signs of arthropathy in immature animals of various species. Ofloxacin, administered systemically at 10 mg/kg/day in young dogs (equivalent to 110 times the maximum recommended daily adult ophthalmic dose) has been associated with these types of effects.

Information for Patients

Avoid contaminating the applicator tip with material from the eye, fingers or other source.

Systemic quinolones, including ofloxacin, have been associated with hypersensitivity reactions, even following a single dose. Discontinue use immediately and contact your physician at the first sign of a rash or allergic reaction.

Drug Interactions

Specific drug interaction studies have not been conducted with OCUFLOX® ophthalmic solution. However, the systemic administration of some quinolones has been shown to elevate plasma concentrations of theophylline, interfere with the metabolism of caffeine, and enhance the effects of the oral anticoagulant warfarin and its derivatives, and has been associated with transient elevations in serum creatinine in patients receiving cyclosporine concomitantly.

Carcinogenesis, Mutagenesis, Impairment of Fertility

Long term studies to determine the carcinogenic potential of ofloxacin have not been conducted.

Ofloxacin was not mutagenic in the Ames test, in vitro and in vivo cytogenic assay, sister chromatid exchange assay (Chinese hamster and human cell lines), unscheduled DNA synthesis (UDS) assay using human fibroblasts, the dominant lethal assay, or mouse micronucleus assay. Ofloxacin was positive in the UDS test using rat hepatocyte, and in the mouse lymphoma assay.

In fertility studies in rats, ofloxacin did not affect male or female fertility or morphological or reproductive performance at oral dosing up to 360 mg/kg/day (equivalent to 4000 times the maximum recommended daily ophthalmic dose).

Pregnancy

Teratogenic Effects

Ofloxacin has been shown to have an embryocidal effect in rats and in rabbits when given in doses of 810 mg/kg/day (equivalent to 9000 times the maximum recommended daily ophthalmic dose) and 160 mg/kg/day (equivalent to 1800 times the maximum recommended daily ophthalmic dose). These dosages resulted in decreased fetal body weight and increased fetal mortality in rats and rabbits, respectively. Minor fetal skeletal variations were reported in rats receiving doses of 810 mg/kg/day. Ofloxacin has not been shown to be teratogenic at doses as high as 810 mg/kg/day and 160 mg/kg/day when administered to pregnant rats and rabbits, respectively.

Nonteratogenic Effects

Additional studies in rats with doses up to 360 mg/kg/day during late gestation showed no adverse effect on late fetal development, labor, delivery, lactation, neonatal viability, or growth of the newborn. There are, however, no adequate and well-controlled studies in pregnant women. OCUFLOX® solution should be used during pregnancy only if the potential benefit justifies the potential risk to the fetus.

Nursing Mothers

In nursing women a single 200 mg oral dose resulted in concentrations of ofloxacin in milk which were similar to those found in plasma. It is not known whether ofloxacin is excreted in human milk following topical ophthalmic administration. Because of the potential for serious adverse reactions from ofloxacin in nursing infants, a decision should be made whether to discontinue nursing or to discontinue the drug, taking into account the importance of the drug to the mother.

Pediatric Use

Safety and effectiveness in infants below the age of one year have not been established.

Quinolones, including ofloxacin, have been shown to cause arthropathy in immature animals after oral administration; however, topical ocular administration of ofloxacin to immature animals has not shown any arthropathy. There is no evidence that the ophthalmic dosage form of ofloxacin has any effect on weight bearing joints.

Geriatric Use

No overall differences in safety or effectiveness have been observed between elderly and younger patients.

ADVERSE REACTIONS

Ophthalmic Use

The most frequently reported drug-related adverse reaction was transient ocular burning or discomfort. Other reported reactions include stinging, redness, itching, chemical conjunctivitis/keratitis, ocular/periocular/facial edema, foreign body sensation, photophobia, blurred vision, tearing, dryness, and eye pain. Rare reports of dizziness and nausea have been received.

Refer to Warnings for additional adverse reactions.

DOSAGE AND ADMINISTRATION

The recommended dosage regimen for the treatment of bacterial conjunctivitis is:

Days 1 and 2 | Instill one to two drops every two to four hours in the affected eye(s).
Days 3 through 7 | Instill one to two drops four times daily.
The recommended dosage regimen for the treatment of bacterial corneal ulcer is:
Days 1 and 2 | Instill one to two drops into the affected eye every 30 minutes, while awake. Awaken at approximately four and six hours after retiring and instill one to two drops.
Days 3 through 7 to 9 | Instill one to two drops hourly, while awake.
Days 7 to 9 through
treatment completion | Instill one to two drops, four times daily.

HOW SUPPLIED

OCUFLOX® (ofloxacin ophthalmic solution) 0.3% is supplied sterile in opaque white LDPE plastic bottles and white dropper tips with tan high impact polystyrene (HIPS) caps as follows:

5mL in 10mL bottle - NDC 11980-779-05

Note: Store at 15°-25°C (59°-77°F)

Rx only

Revised: 06/2024

Distributed by:
AbbVie, Inc.
North Chicago, IL 60064

© 2024 AbbVie. All rights reserved.
Ocuflox and its design are trademarks of Allergan, Inc., an AbbVie company.

20085528

PRINCIPAL DISPLAY PANEL

NDC 11980-779-05
5 mL
Ocuflox®
(ofloxacin ophthalmic solution) 0.3%
Rx only
Sterile
abbvie